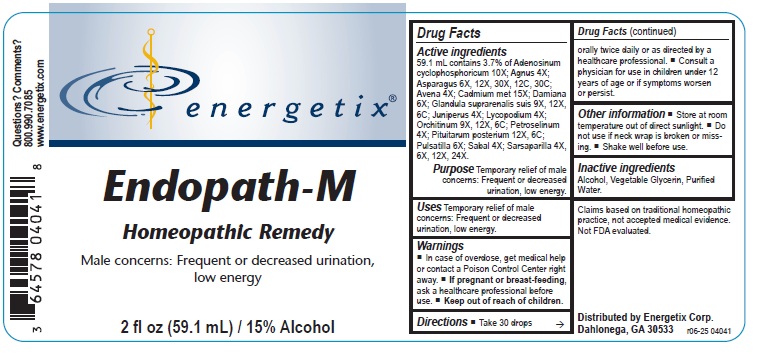 DRUG LABEL: Endopath-M
NDC: 64578-0099 | Form: LIQUID
Manufacturer: Energetix Corporation
Category: homeopathic | Type: HUMAN OTC DRUG LABEL
Date: 20251222

ACTIVE INGREDIENTS: ADENOSINE CYCLIC PHOSPHATE 10 [hp_X]/1 mL; CHASTE TREE 4 [hp_X]/1 mL; ASPARAGUS 6 [hp_X]/1 mL; AVENA SATIVA FLOWERING TOP 4 [hp_X]/1 mL; CADMIUM 15 [hp_X]/1 mL; TURNERA DIFFUSA LEAFY TWIG 6 [hp_X]/1 mL; SUS SCROFA ADRENAL GLAND 9 [hp_X]/1 mL; JUNIPER BERRY 4 [hp_X]/1 mL; LYCOPODIUM CLAVATUM SPORE 4 [hp_X]/1 mL; BOS TAURUS TESTICLE 9 [hp_X]/1 mL; PETROSELINUM CRISPUM 4 [hp_X]/1 mL; SUS SCROFA PITUITARY GLAND 12 [hp_X]/1 mL; PULSATILLA VULGARIS 6 [hp_X]/1 mL; SAW PALMETTO 4 [hp_X]/1 mL; SMILAX ORNATA ROOT 4 [hp_X]/1 mL
INACTIVE INGREDIENTS: WATER; ALCOHOL; GLYCERIN

Endopath-M

ACTIVE INGREDIENT

Active ingredients59.1 mL contains 3.7% of Adenosinum cyclophosphoricum 10X; Agnus 4X; Asparagus 6X, 12X, 30X, 12C, 30C;
Avena 4X; Cadmium met 15X; Damiana 6X; Glandula suprarenalis suis 9X, 12X, 6C; Juniperus 4X; Lycopodium 4X; Orchitinum 9X,
12X, 6C; Petroselinum 4X; Pituitarum posterium 12X, 6C; Pulsatilla 6X; Sabal 4X; Sarsaparilla 4X, 6X, 12X, 24X

Claims based on traditional homeopathic practice, not accepted medical evidence. Not FDA evaluated.

INDICATIONS AND USAGE

UsesTemporary relief of male concerns: Frequent or decreased urination, low energy.

Warnings

- In case of overdose, get medical help or contact a Poison Control Center right away.
- If pregnant or breast-feeding, ask a healthcare professional before use.

Keep out of reach of children.

Directions

- Take 30 drops orally twice daily or as directed by a healthcare professional.
- Consult a physician for use in children under 12 years of age or if symptoms worsen or persist.

Other information

- Store at room temperature out of direct sunlight.
- Do not use if neck wrap is broken or missing.
- Shake well before use.

Inactive ingredients Alcohol, Vegetable Glycerin, Purified Water.

QUESTIONS

Distributed by Energetix Corp.
Dahlonega, GA 30533
Questions? Comments?

800.990.7085
www.energetx.com

PACKAGE LABEL

energetix

Endopath-M

Homeopathic Remedy

Male concerns: Frequent or decreased urination,

low energy

2 fl oz (59.1 mL) / 15% Alcohol

PURPOSE

PurposeTemporary relief of male concerns: Frequent or decreased urination, low energy.